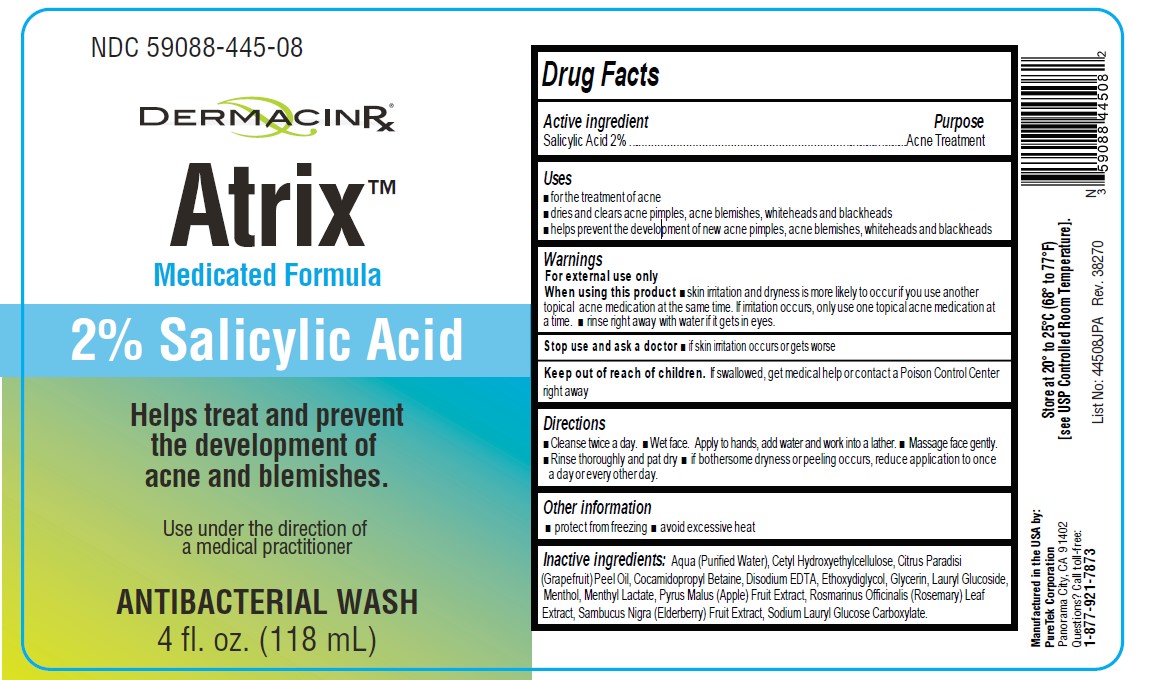 DRUG LABEL: Atrix Antibacterial  Wash
NDC: 59088-445 | Form: LIQUID
Manufacturer: PURETEK CORPORATION
Category: otc | Type: HUMAN OTC DRUG LABEL
Date: 20241001

ACTIVE INGREDIENTS: SALICYLIC ACID 20 mg/1 mL
INACTIVE INGREDIENTS: WATER; CETYL HYDROXYETHYLCELLULOSE (350000 MW); GRAPEFRUIT OIL; COCAMIDOPROPYL BETAINE; EDETATE DISODIUM; DIETHYLENE GLYCOL MONOETHYL ETHER; GLYCERIN; LAURYL GLUCOSIDE; MENTHOL, UNSPECIFIED FORM; MENTHYL LACTATE, (-)-; APPLE; ROSEMARY; EUROPEAN ELDERBERRY; SODIUM LAURYL GLYCOL CARBOXYLATE

Atrix™ Antibacterial Wash

Drug Facts

Active ingredient

Salicylic Acid 2%

Purpose

Acne treatment

Use

■ for the treatment of acne

■ dries and clears acne pimples, acne blemishes, whiteheads, and blackheads

■ helps prevent the development of new acne pimples, acne blemishes, whiteheads, and blackheads

Warnings

For external use only.

When using this product

■ skin irritation and dryness is more likely to occur if you use another topical acne medication at the same time. If irritation occurs, only use one topical acne medication at a time.

■ rinse right away with water if it gets in eyes.

Stop use and ask a doctor

■ if skin irritation occurs or gets worse

Keep out of reach of children.

If swallowed, get medical help or contact a Poison Control Center right away.

Directions

■ Cleanse twice a day.

■ Wet face. Apply to hands, add water and work into a lather.

■ Massage face gently.
■ Rinse thoroughly and pat dry if bothersome dryness or peeling occurs, reduce application to once a day or every other day.

Use under the direction of a medical practitioner.

Other information

■ protect from freezing

■ avoid excessive heat

Store at 20° to 25°C (68° to 77°F)
[see USP Controlled Room Temperature].

Inactive ingredients

Aqua (Purified Water), Cetyl Hydroxyethylcellulose, Citrus Paradisi (Grapefruit) Peel Oil, Cocamidopropyl Betaine, Disodium EDTA, Ethoxydiglycol, Glycerin, Lauryl Glucoside, Menthol, Menthyl Lactate, Pyrus Malus (Apple) Fruit Extract, Rosmarinus Officinalis (Rosemary) Leaf Extract, Sambucus Nigra (Elderberry) Fruit Extract, Sodium Lauryl Glucose Carboxylate.

Questions?

Call toll-free:

1-877-921-7873

Atrix™ Antibacterial Wash

Manufactured in the USA by:
PureTek Corporation
Panorama City, CA 91402
Questions? Call toll-free:
1-877-921-7873